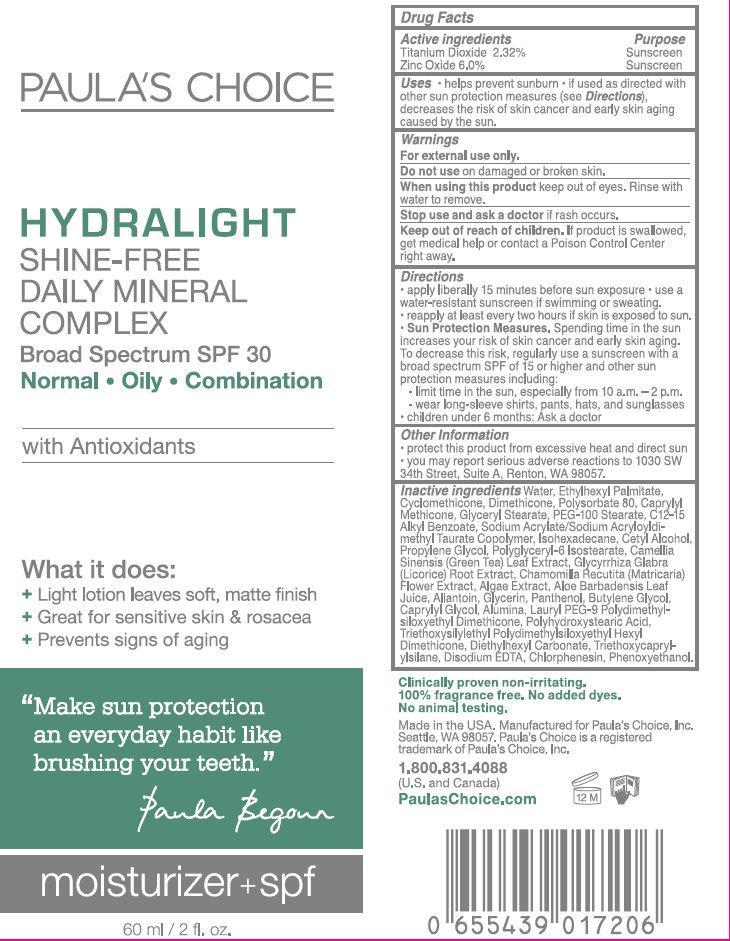 DRUG LABEL: PAULAS CHOICE HYDRALIGHT SHINE-FREE DAILY MINERAL COMPLEX Broad Spectrum SPF 30
NDC: 76144-000 | Form: LOTION
Manufacturer: Paula's Choice, Inc
Category: otc | Type: HUMAN OTC DRUG LABEL
Date: 20250131

ACTIVE INGREDIENTS: TITANIUM DIOXIDE 23.2 mg/1 mL; ZINC OXIDE 60 mg/1 mL
INACTIVE INGREDIENTS: GLYCERYL MONOSTEARATE; PEG-100 STEARATE; ALKYL (C12-15) BENZOATE; ISOHEXADECANE; CETYL ALCOHOL; PROPYLENE GLYCOL; GREEN TEA LEAF; GLYCYRRHIZA GLABRA; CHAMOMILE; ALOE VERA LEAF; ALLANTOIN; GLYCERIN; PANTHENOL; BUTYLENE GLYCOL; CAPRYLYL GLYCOL; ALUMINUM OXIDE; LAURYL PEG-9 POLYDIMETHYLSILOXYETHYL DIMETHICONE; DIETHYLHEXYL CARBONATE; TRIETHOXYCAPRYLYLSILANE; EDETATE DISODIUM; CHLORPHENESIN; PHENOXYETHANOL; WATER; ETHYLHEXYL PALMITATE; CYCLOMETHICONE; DIMETHICONE; POLYSORBATE 80; CAPRYLYL TRISILOXANE

PAULA'S CHOICE HYDRALIGHT SHINE-FREE DAILY MINERAL COMPLEX Broad Spectrum SPF 30

Active Ingredients

Titanium Dioxide 2.32% Zinc Oxide 6.0%

Purpose

Sunscreen

Uses

- helps prevent sunburn
- if used as directed with other sun protection measures (see), decreases the risk of skin cancer and early skin aging caused by the sun. Directions

Warnings

For external use only.

Do not use

on damaged or broken skin.

When using this product

keep out of eyes. Rinse with water to remove.

Stop use and ask a doctor

if rash occurs.

KEEP OUT OF REACH OF CHILDREN

If product is swallowed, get medical help or contact a Poison Control Center right away.

DOSAGE AND ADMINISTRATION

- apply liberally 15 minutes before sun exposure
- use a water-resistant sunscreen if swimming or sweating.
- reapply at least every two hours if skin exposed to sun.
- Spending time in the sun increases your risk of skin cancer and early skin aging. To decrease this risk, regularly use a sunscreen with a broad spectrum SPF of 15 or higher and other sun protection measures including: Sun Protection Measures.
-
  - limit time in the sun, especially from 10 a.m. - 2 p.m.
  - wear long-sleeve shirts, pants, hats, and sunglasses
- children under 6 months: Ask a doctor

Other Information

- protect this product from excessive heat and direct sun
- you may report serious and adverse reactions to 1030 SW 34th Street, Suite A, Renton, WA 98057

Inactive Ingredients

Water, Ethylhexyl Palmitate, Cyclomethicone, Dimethicone, Polysorbate 80, Caprylyl Methicone, Glyceryl Stearate, PEG-100 Stearate, C12-15 Alkyl Benzoate, Sodium Acrylate/Sodium Acryloyldimethyl Taurate Copolymer, Isohexadecane, Cetyl Alcohol, Propylene Glycol, Polyglyceryl-6 Isostearate, Camellia Sinensis (Green Tea) Leaf Extract, Glycyrrhiza Glabra (Licorice) Root Extract, Chamomila Recutita (Matricaria) Flower Extract, Algae Extract, Aloe Barbadensis Leaf Juice, Allantoin, Glycerin, Panthenol, Butylene Glycol, Caprylyl Glycol, Alumina, Lauryl PEG-9 Polydimethylsiloxyethyl Dimethicone, Polyhydroxystearic Acid, Triethoxysilylethyl Polydimethylsiloxyethyl Hexyl Dimethicone, Diethylhexyl Carbonate, Triethoxycaprylylsilane, Disodium EDTA, Chlorphenesin, Phenoxyethanol.

What it does:

* Light lotion leaves soft, matte finish * Great for sensitive skin and rosacea * Prevents signs of aging "Make sun protection an every day habit like brushing your teeth." Paula Begour Clinically proven non-irritating. 100% fragrance free. No added dyes. No animal testing. Made in USA. Manufactured for Paula's Choice, Inc. Seattle, WA 98057. Paula's Choice is a registered trademark of Paula's Choice, Inc. 1.800.831.4088 (U.S. and Canada) PaulasChoice.com

PACKAGE LABEL

PAULA'S CHOICE HYDRALIGHT SHINE-FREE DAILY MINERAL COMPLEX Broad Spectrum SPF 30 Normal Oily Combination with Antioxidants moisturizer + spf 60 ml / 2 fl. oz.